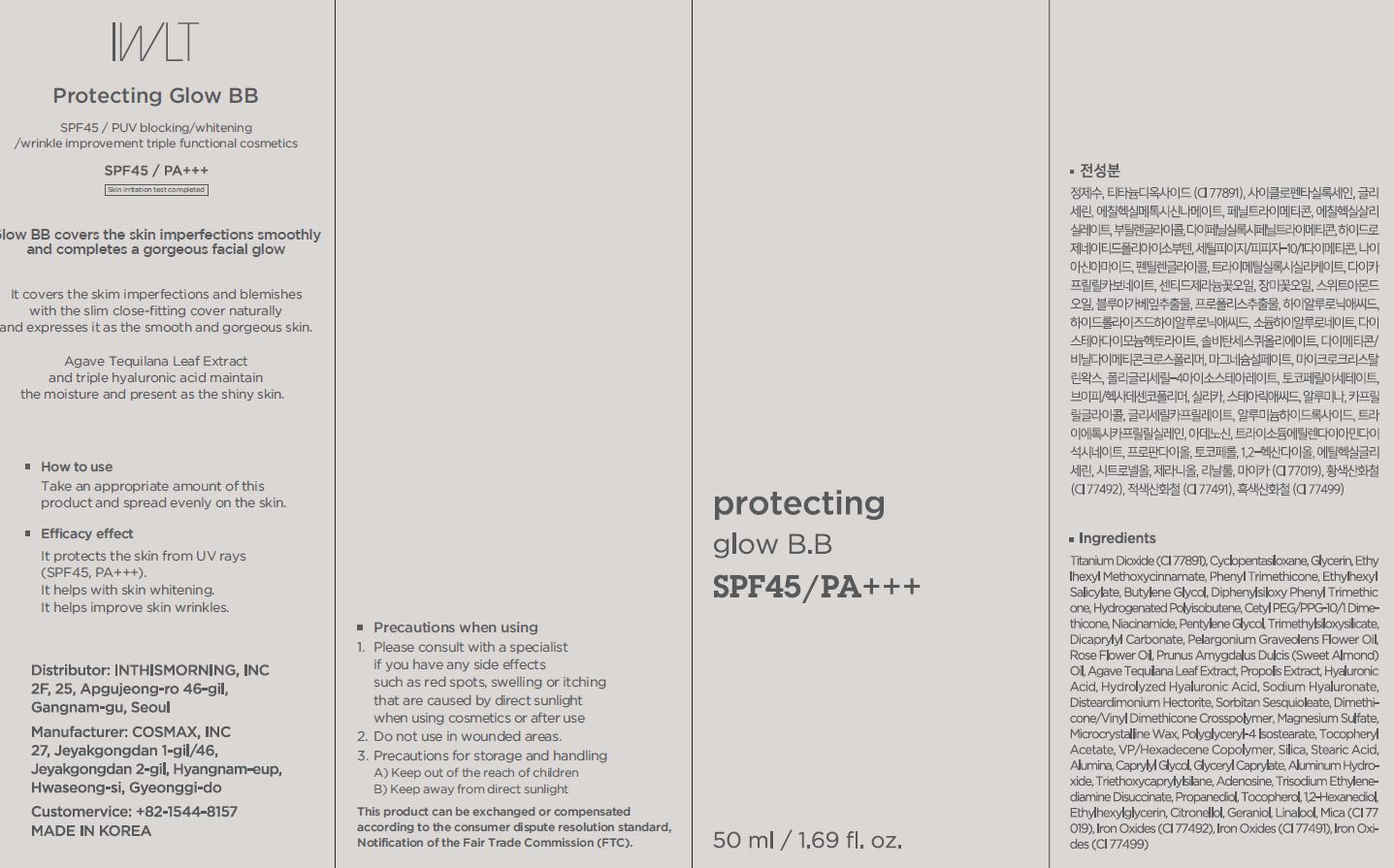 DRUG LABEL: Protecting tone up and glow B.B
NDC: 71217-0061 | Form: CREAM
Manufacturer: inthismorning co ltd
Category: otc | Type: HUMAN OTC DRUG LABEL
Date: 20230130

ACTIVE INGREDIENTS: NIACINAMIDE 2 g/100 mL; ADENOSINE 0.04 g/100 mL
INACTIVE INGREDIENTS: WATER; GLYCERIN

Drug Facts

ACTIVE INGREDIENT

niacinamide, adenosine

INACTIVE INGREDIENT

Water, glycerin, etc

PURPOSE

skin whitening, improve skin wrinkles

keep out or reach of the children

INDICATIONS AND USAGE

take an appropriate amount of this product and spread evenly on the skin

WARNINGS

This product is for exeternal use only. Do not use for internal use
Storage and handling precautions
If possible, avoid direct sunlight and store in cool and area of low humidity in order to maintain the quality of the product and avoid misuse
Avoid placing the product near fire and store out in reach of children

- consult a physician in case of abnormal symptoms, such as red spots, swelling or itching, or side effects in the areas of application due to direct light during or after using the product

- do not use on wounded area

DOSAGE AND ADMINISTRATION

for external use only